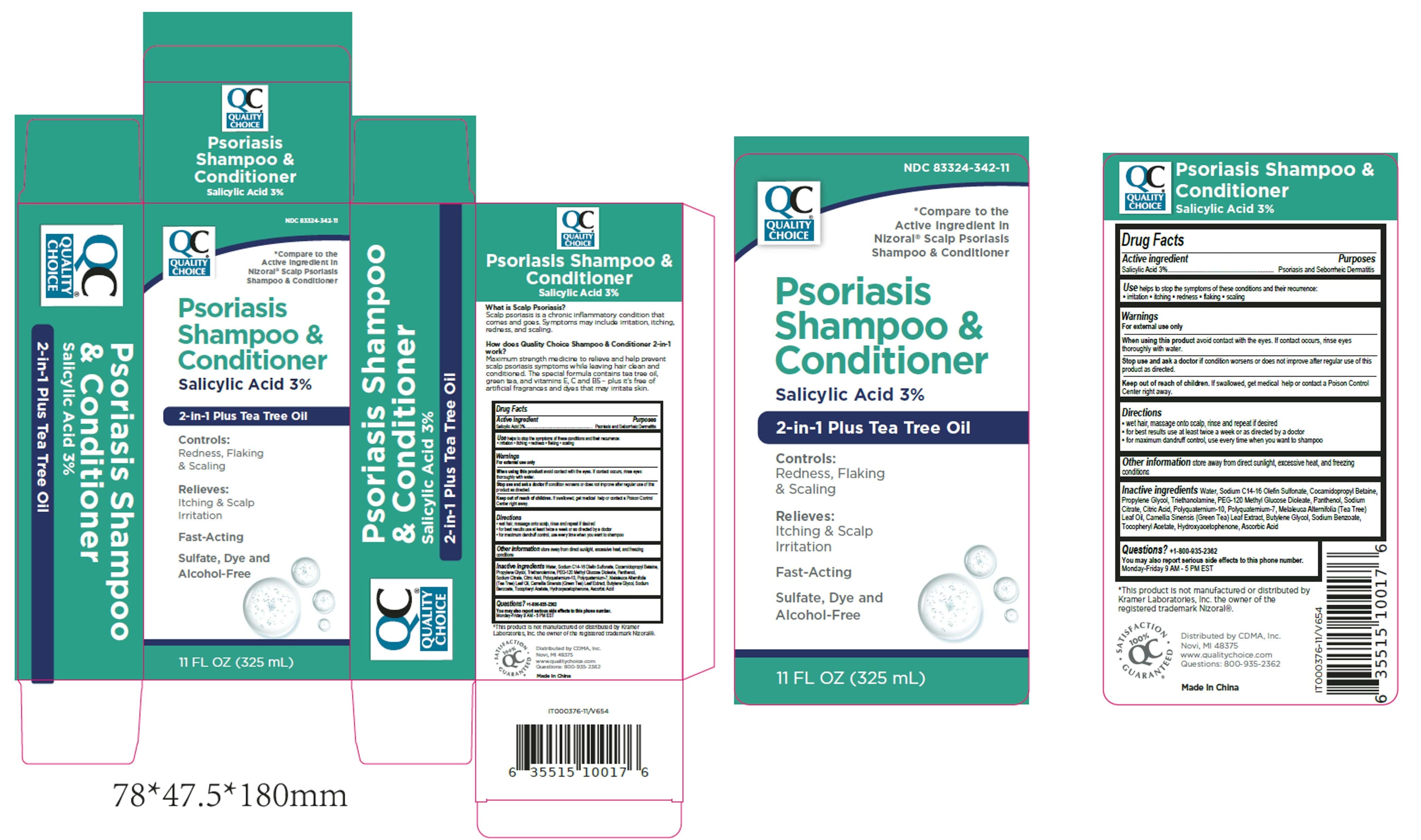 DRUG LABEL: Quality Choice Psoriasis
NDC: 83324-342 | Form: SHAMPOO
Manufacturer: Chain Drug Marketing Association, Inc.
Category: otc | Type: HUMAN OTC DRUG LABEL
Date: 20251223

ACTIVE INGREDIENTS: SALICYLIC ACID 3 g/100 mL
INACTIVE INGREDIENTS: WATER; SODIUM C14-16 OLEFIN SULFONATE; COCAMIDOPROPYL BETAINE; PROPYLENE GLYCOL; TRIETHANOLAMINE; PEG-120 METHYL GLUCOSE DIOLEATE; PANTHENOL; SODIUM CITRATE; CITRIC ACID; POLYQUATERNIUM-10 (1000 MPA.S AT 2%); POLYQUATERNIUM-7; MELALEUCA ALTERNIFOLIA (TEA TREE) LEAF OIL; CAMELLIA SINENSIS LEAF; BUTYLENE GLYCOL; SODIUM BENZOATE; .ALPHA.-TOCOPHEROL ACETATE; HYDROXYACETOPHENONE; ASCORBIC ACID

QC Psoriasis Shampoo & Conditioner - Longway

Active Ingredient

Salicylic Acid 3%

Purpose

Psoriasis and Seborrheic Dermatitis

Uses

helps to stop the symptoms of these conditions and their recurrence: ▪ irritation ▪ itching ▪ redness ▪ flaking ▪ scaling

WARNINGS

WarningsFor external use only

When using this product

avoid contact with the eyes. If contact occurs, rinse eyes thoroughly with water.

Stop use and ask doctor if

condition worsens or does not improve after regular use of this
product as directed.

KEEP OUT OF REACH OF CHILDREN

Keep out of the reach of children. If swallowed, get medical help or contact a Poison Control
Center right away.

Directions

▪ wet hair, massage onto scalp, rinse and repeat if desired
▪ for best results use at least twice a week or as directed by a doctor
▪ for maximum dandruff control, use every time when you want to shampoo

Other information

store away from direct sunlight, excessive heat, and freezing conditions

Inactive ingredients

Water, Sodium C14-16 Olefin Sulfonate, Cocamidopropyl Betaine,
Propylene Glycol, Triethanolamine, PEG-120 Methyl Glucose Dioleate, Panthenol, Sodium
Citrate, Citric Acid, Polyquaternium-10, Polyquaternium-7, Melaleuca Alternifolia (Tea Tree)
Leaf Oil, Camellia Sinensis (Green Tea) Leaf Extract, Butylene Glycol, Sodium Benzoate,
Tocopheryl Acetate, Hydroxyacetophenone, Ascorbic Acid

Questions? +1-800-935-2362
You may also report serious side effects to this phone number.
Monday-Friday 9 AM - 5 PM EST